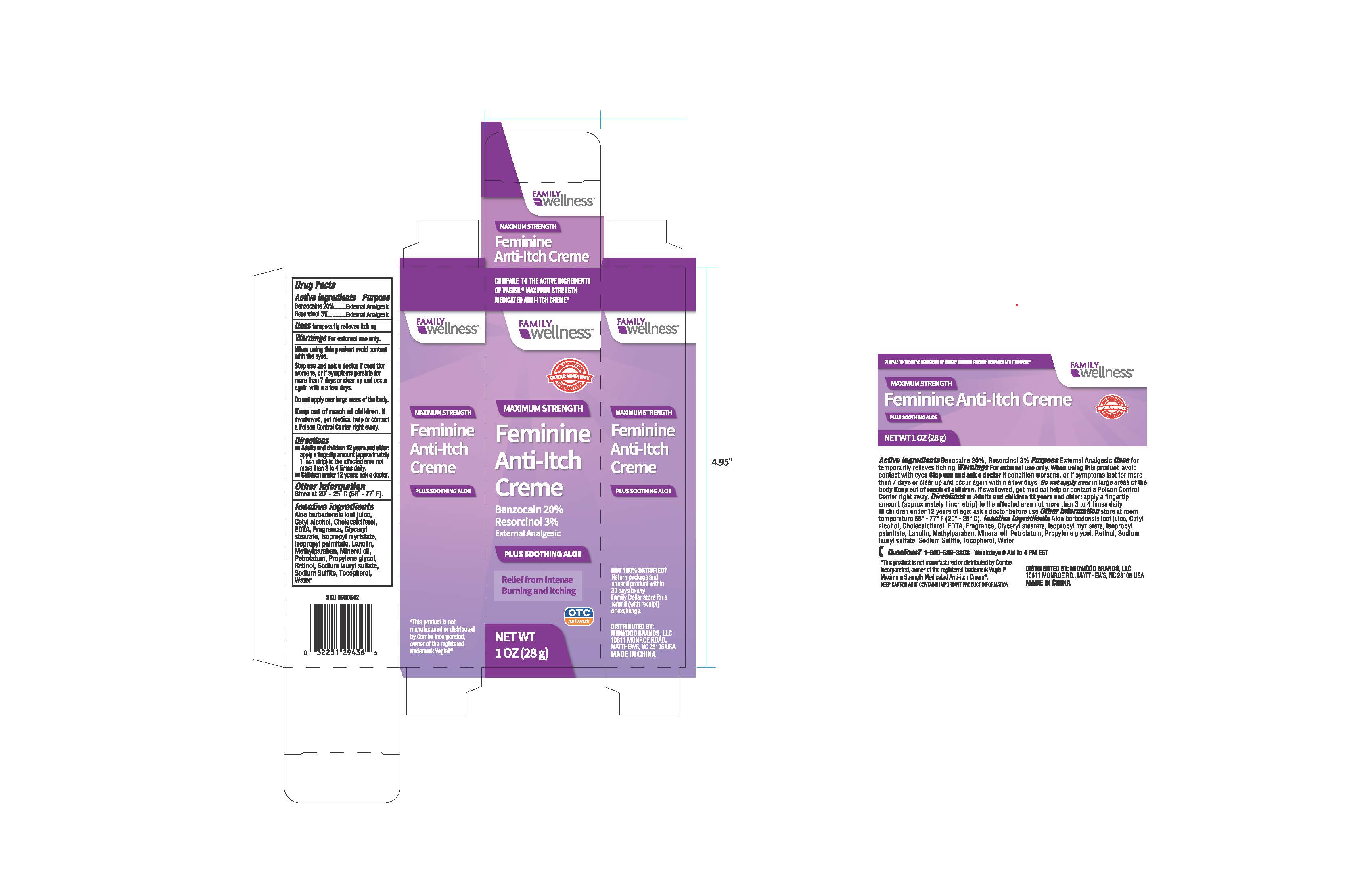 DRUG LABEL: Family Wellness
NDC: 55621-016 | Form: CREAM
Manufacturer: Zhejiang Jingwei Pharmaceutic Al Co., Ltd.
Category: otc | Type: HUMAN OTC DRUG LABEL
Date: 20231027

ACTIVE INGREDIENTS: BENZOCAINE 20 g/100 g; RESORCINOL 3 g/100 g
INACTIVE INGREDIENTS: ISOPROPYL PALMITATE; LANOLIN; METHYLPARABEN; MINERAL OIL; PETROLATUM; PROPYLENE GLYCOL; RETINOL; SODIUM LAURYL SULFATE; SODIUM SULFATE; TOCOPHEROL; WATER; ALOE VERA LEAF; CETYL ALCOHOL; CHOLECALCIFEROL; EDETIC ACID; GLYCERYL MONOSTEARATE; ISOPROPYL MYRISTATE

Active ingredients

Benzocaine 20%

Resorcinol 3%

Purpose

External Analgesic

External Analgesic

INDICATIONS AND USAGE

temporarily relieves itching Uses

. Warnings For external use only

avoid contact When using this product

with the eyes.

if condition Stop use and ask a doctor

worsens, or if symptoms persists for

more than 7 days or clear up and occur

again within a few days.

over large areas of the body. Do not apply

. If Keep out of reach of children

swallowed, get medical help or contact

a Poison Control Center right away.

Directions

• Adults and children 12 years and older:

apply a fingertip amount (approximately

1 inch strip) to the affected area not

more than 3 to 4 times daily.

•: ask a doctor Children udner 12 years

Other information

Atore at 20° - 25° C (68° - 77° F).

Inactive ingredients

Aloe barbadensis leaf juice,

Cetyl alcohol, Cholecalciferol,

EDTA, Fragrance, Glyceryl

stearate, Isopropyl myristate,

Isopropyl palmitate, Lanolin,

Methylparaben, Mineral Oil,

Petrolatum, Propylene glycol,

Retinol, Sodium lauryl sulfate,

Sodium Sulfate, Tocopherol,

Water